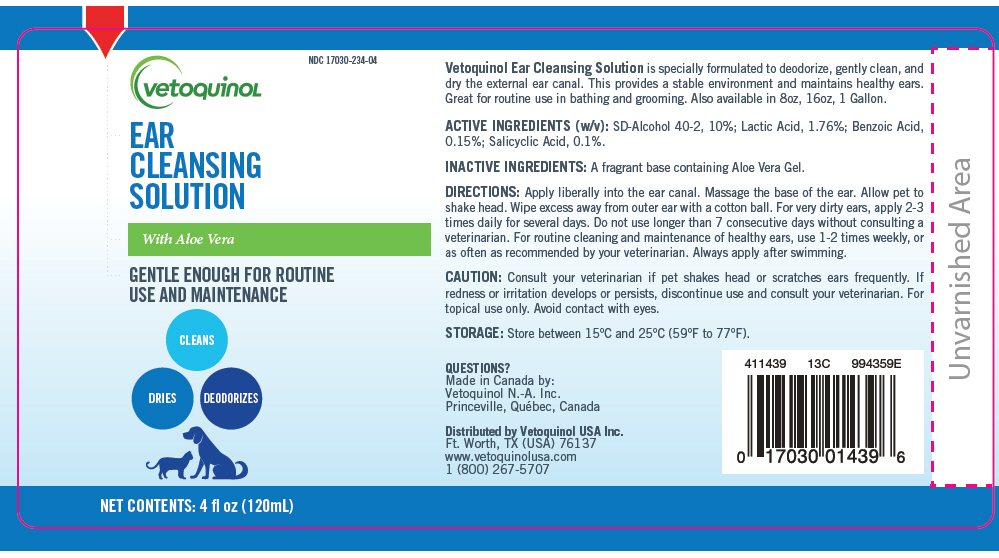 DRUG LABEL: Ear Cleansing
NDC: 17030-234 | Form: LIQUID
Manufacturer: Vetoquinol USA, Inc.
Category: animal | Type: OTC ANIMAL DRUG LABEL
Date: 20190816

ACTIVE INGREDIENTS: Alcohol 11.08 mL/1 mL; Lactic Acid, Unspecified Form 17.6 mg/1 mL; Benzoic Acid 1.5 mg/1 mL; Salicylic Acid 1 mg/1 mL
INACTIVE INGREDIENTS: Tert-Butyl Alcohol; Brucine Sulfate; Water; Propylene Glycol; Aloe Vera Leaf; DOCUSATE SODIUM; Glycerin; Benzyl Alcohol

EAR CLEANSING SOLUTION

VETERINARY INDICATIONS

Vetoquinol Ear Cleansing Solution is specially formulated to deodorize, gently clean, and dry the external ear canal. This provides a stable environment and maintains healthy ears. Great for routine use in bathing and grooming. Also available in 8oz, 16oz, 1 Gallon.

ACTIVE INGREDIENTS (w/v): SD-Alcohol 40-2, 10%; Lactic Acid, 1.76%; Benzoic Acid, 0.15%; Salicyclic Acid, 0.1%.

INACTIVE INGREDIENTS: A fragrant base containing Aloe Vera Gel.

DOSAGE AND ADMINISTRATION

DIRECTIONS: Apply liberally into the ear canal. Massage the base of the ear. Allow pet to shake head. Wipe excess away from outer ear with a cotton ball. For very dirty ears, apply 2-3 times daily for several days. Do not use longer than 7 consecutive days without consulting a veterinarian. For routine cleaning and maintenance of healthy ears, use 1-2 times weekly, or as often as recommended by your veterinarian. Always apply after swimming.

WARNINGS

CAUTION: Consult your veterinarian if pet shakes head or scratches ears frequently. If redness or irritation develops or persists, discontinue use and consult your veterinarian. For topical use only. Avoid contact with eyes.

STORAGE AND HANDLING

STORAGE: Store between 15°C and 25°C (59°F to 77°F).

QUESTIONS?
Made in Canada by:
Vetoquinol N.-A. Inc.
Princeville, Québec, Canada

Distributed by Vetoquinol USA Inc.
Ft. Worth, TX (USA) 76137
www.vetoquinolusa.com
1 (800) 267-5707

411439
13C
994359E

PRINCIPAL DISPLAY PANEL - 120 mL Bottle Label

NDC 17030-234-04

vetoquinoL

EAR
CLEANSING
SOLUTION

With Aloe Vera

GENTLE ENOUGH FOR ROUTINE
USE AND MAINTENANCE

CLEANS
DRIES
DEODORIZES

NET CONTENTS: 4 fl oz (120mL)